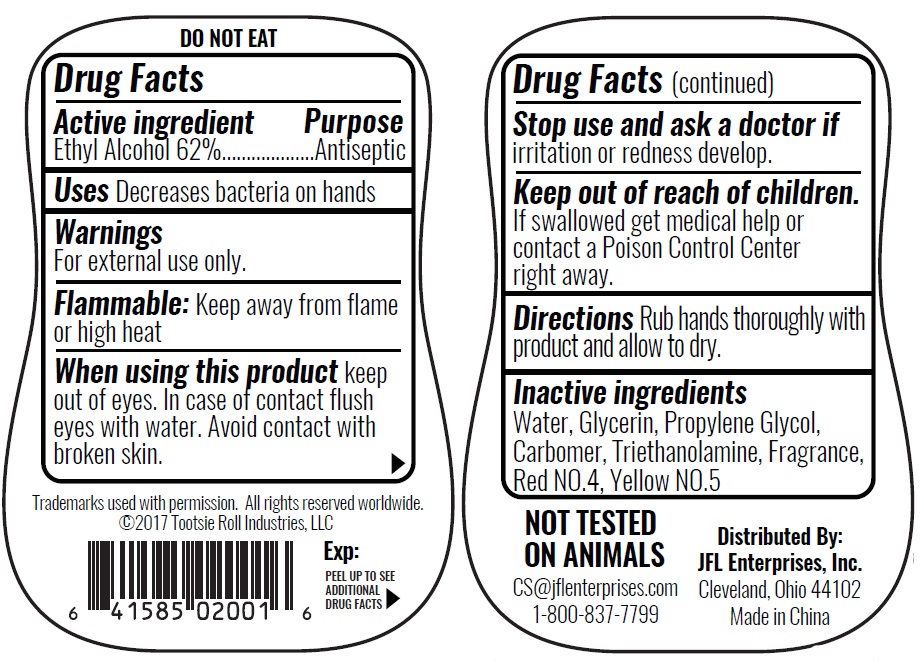 DRUG LABEL: Hand Sanitizer Orange
NDC: 71246-4024 | Form: GEL
Manufacturer: JFL ENTERPRISES, INC
Category: otc | Type: HUMAN OTC DRUG LABEL
Date: 20180101

ACTIVE INGREDIENTS: ALCOHOL 62 mL/100 mL
INACTIVE INGREDIENTS: CARBOMER HOMOPOLYMER TYPE B (ALLYL SUCROSE CROSSLINKED); FD&C YELLOW NO. 5; FD&C RED NO. 4; GLYCERIN; ORANGE; PROPYLENE GLYCOL; TRIETHANOLAMINE 2-CYCLOHEXYL-4,6-DINITROPHENOLATE; WATER

ANTIBACTERIAL HAND GEL Tootsie Orange

Active ingredient

Alcohol 62%

Purpose

Antiseptic Hand Sanitizer

Use

Decrease bacteria on hands

Warnings

External Use Only. DO NOT EAT.

Keep out of reach of children

if swallowed get medical help or contact a Poison Control Center right away.

WARNINGS

Flammable: Keep away from flame or high heat

Directions

Rub hands thoroughly with product and allow to dry.

Inactive Ingredient

Water, Glycerin, Propylene Glycol, Carbomer, Triethanolamine, Fragrance,Yellow NO. 5, Red NO. 4

Stop and Ask a doctor if

Irritation or redness develop.